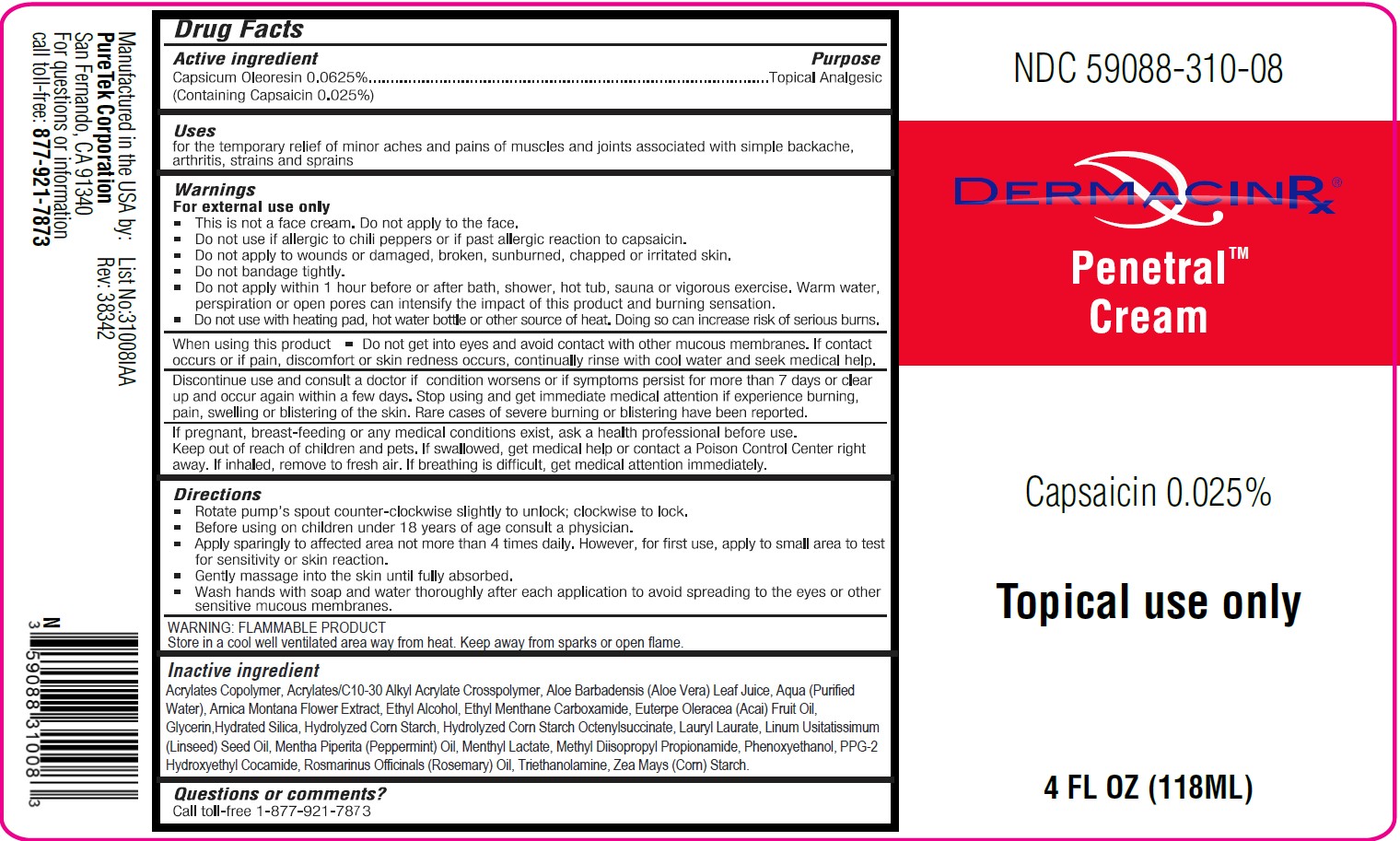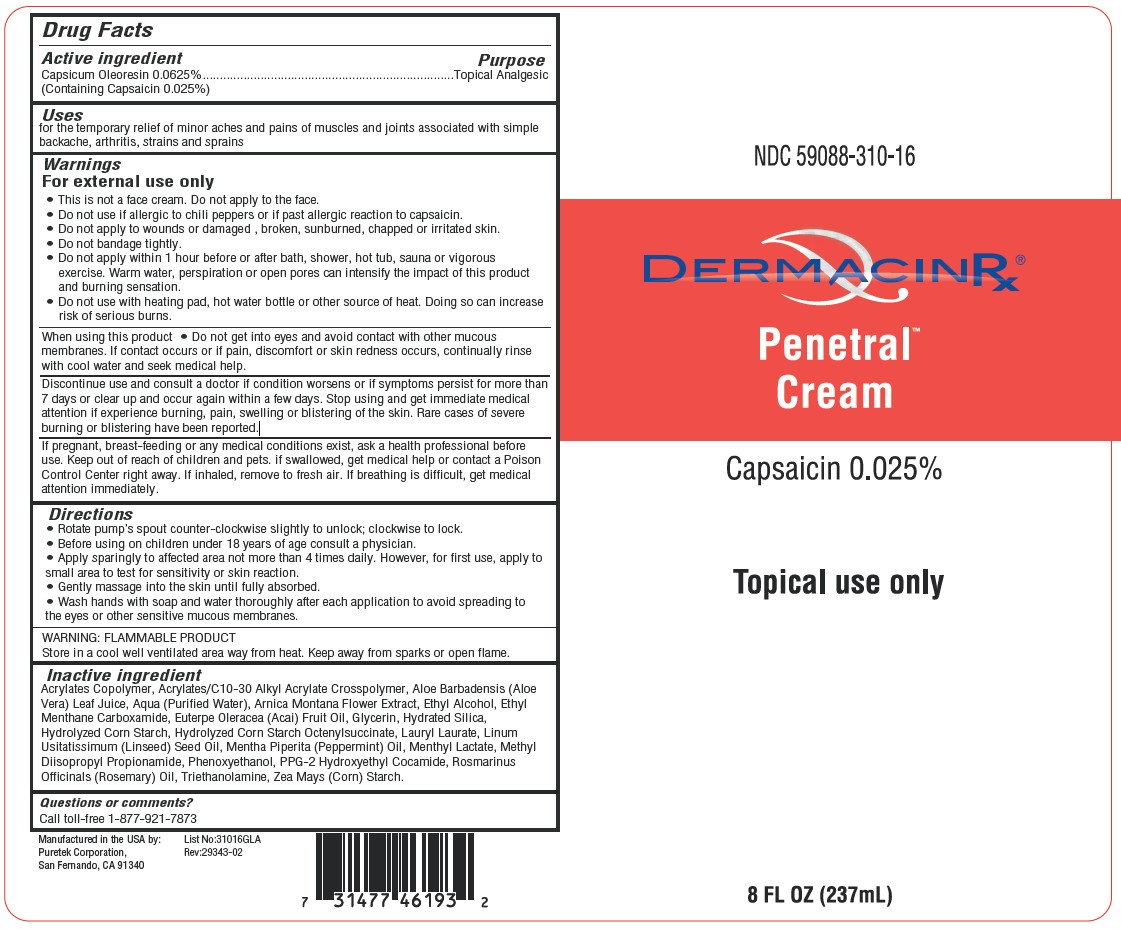 DRUG LABEL: DermacinRx Penetral Cream
NDC: 59088-310 | Form: CREAM
Manufacturer: PureTek Corporation
Category: otc | Type: HUMAN OTC DRUG LABEL
Date: 20241002

ACTIVE INGREDIENTS: CAPSICUM OLEORESIN 0.25 mg/1 mL
INACTIVE INGREDIENTS: STARCH, CORN; HYDROXYETHYL BEHENAMIDOPROPYL DIMONIUM CHLORIDE; LAURYL LAURATE; TROLAMINE; METHACRYLIC ACID - ETHYL ACRYLATE COPOLYMER (1:1) TYPE A; WATER; ALOE VERA LEAF; ARNICA MONTANA FLOWER; ALCOHOL; ETHYL MENTHANE CARBOXAMIDE; ACAI OIL; HYDRATED SILICA; GLYCERIN; CORN SYRUP; PEPPERMINT OIL; MENTHYL LACTATE, (-)-; METHYL DIISOPROPYL PROPIONAMIDE; PHENOXYETHANOL; PPG-2 HYDROXYETHYL COCAMIDE; ROSEMARY OIL; CARBOMER INTERPOLYMER TYPE A (55000 CPS); OCTENYLSUCCINIC ANHYDRIDE; AMYLOPECTIN, UNSPECIFIED SOURCE; LINSEED OIL

Penetral Cream
10/14- added new size 118 mL
10/19-Updating marketing date for new size 118ml

Active ingredient

Capsicum Oleoresin 0.0625% (Containing Capsaicin 0.025%)

Purpose

Topical Analgesic

Uses

for the temporary relief of minor aches and pains of muscles and joints associated with simple backache, arthritis, strains and sprains

Warnings

For external use only

DO NOT USE

- This is not a face cream. Do not apply to the face.
- Do not use if allergic to chili peppers or if past allergic reaction to capsaicin.
- Do not apply to wounds or damaged, broken, sunburned, chapped or irritated skin.
- Do not bandage tightly.
- Do not apply within 1 hour before or after bath, shower, hot tub, sauna or vigorous exercise. Warm water, perspiration or open pores can intensify the impact of this product and cause a burning sensation.
- Do not use with heating pad, hot water bottle or other source of heat. Doing so can increase risk of serious burns.

When using this product

do not get into eyes and avoid contact with other mucous membranes. If contact occurs or if pain, discomfort or skin redness occurs, continually rinse with cool water and seek medical help.

Discontinue use and consult a doctor if

condition worsens or if symptoms persist for more than 7 days or clear up and occur again within a few days. Stop using and get immediate medical attention if experience burning, pain, swelling or blistering of the skin. Rare cases of severe burning or blistering have been reported. If pregnant, breast-feeding or any medical conditions exist, ask a health professional before use.

Keep out of reach of children and pets.

If swallowed, get medical help or contact a Poison Control Center right away. If inhaled, remove to fresh air. If breathing is difficult, get medical attention immediately.

Directions

- Rotate pump’s spout counter-clockwise slightly to unlock; clockwise to lock.
- Before using on children under 18 years of age, consult a physician.
- Apply sparingly to affected area not more than 4 times daily. However, for first use, apply to small area to test for sensitivity or skin reaction.
- Gently massage into the skin until fully absorbed.
- Wash hands with soap and water thoroughly after each application to avoid spreading to the eyes or other sensitive mucous membranes.

Other information

WARNING: FLAMMABLE PRODUCT
Store in a cool well ventilated area away from heat. Keep away from sparks or open flame.

Inactive ingredients

Acrylates Copolymer, Acrylates/C10-30 Alkyl Acrylate Crosspolymer, Aloe Barbadensis (Aloe Vera) Leaf Juice, Aqua (Purified Water), Arnica Montana Flower Extract, Ethyl Alcohol, Ethyl Menthane Carboxamide, Euterpe Oleracea (Acai) Fruit Oil, Glycerin,Hydrated Silica, Hydrolyzed Corn Starch, Hydrolyzed Corn Starch Octenylsuccinate, Lauryl Laurate, Linum Usitatissimum (Linseed) Seed Oil, Mentha Piperita (Peppermint) Oil, Menthyl Lactate, Methyl Diisopropyl Propionamide, Phenoxyethanol, PPG-2 Hydroxyethyl Cocamide, Rosmarinus Officinals (Rosemary) Oil, Triethanolamine, Zea Mays (Corn) Starch.

Questions or comments?

Call toll-free 1-877-921-7873 or visit us at www.dermacinrx.com